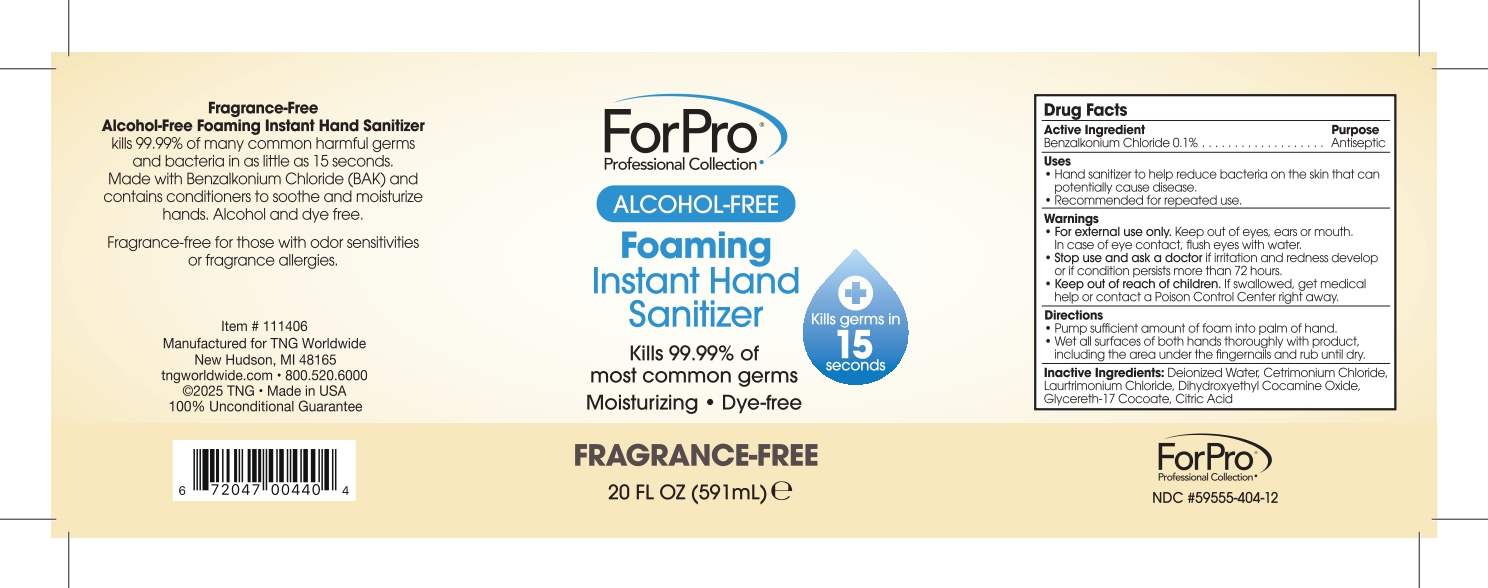 DRUG LABEL: ForPro Professional Collection Alcohol-Free Foaming Instant Hand Sanitizer
NDC: 59555-404 | Form: LIQUID
Manufacturer: R & R Lotion, Inc
Category: otc | Type: HUMAN OTC DRUG LABEL
Date: 20260211

ACTIVE INGREDIENTS: BENZALKONIUM CHLORIDE 1 mg/1 mL
INACTIVE INGREDIENTS: WATER; CETRIMONIUM CHLORIDE; LAURTRIMONIUM CHLORIDE; DIHYDROXYETHYL COCAMINE OXIDE; GLYCERETH-17 COCOATE; CITRIC ACID MONOHYDRATE

ForPro® Professional Collection Alcohol-Free Foaming Instant Hand Sanitizer - Fragrance-Free

Drug Facts

Active Ingredient

Benzalkonium Chloride 0.1%

Purpose

Antiseptic

Uses

- Hand sanitizer to help reduce bacteria on the skin that can potentially cause disease.
- Recommended for repeated use.

Warnings

- For external use only. Keep out of eyes, ears or mouth. In case of eye contact, flush eyes with water.

- Stop use and ask a doctor if irritation and redness develop or if condition persists more than 72 hours.

- Keep out of reach of children. If swallowed, get medical help or contact a Poison Control Center right away.

Directions

- Pump sufficient amount of foam into palm of hand.
- Wet all surfaces of both hands thoroughly with product, including the area under the fingernails and rub until dry.

Inactive Ingredients:

Deionized Water, Cetrimonium Chloride, Laurtrimonium Chloride, Dihydroxyethyl Cocamine Oxide, Glycereth-17 Cocoate, Citric Acid

PRINCIPAL DISPLAY PANEL - 591 mL Bottle Label

ForPro®
Professional Collection

ALCOHOL-FREE

Foaming
Instant Hand
Sanitizer

Kills germs in
15
seconds

Kills 99.99% of
most common germs

Moisturizing • Dye-free

FRAGRANCE-FREE

20 FL OZ (591mL) ℮